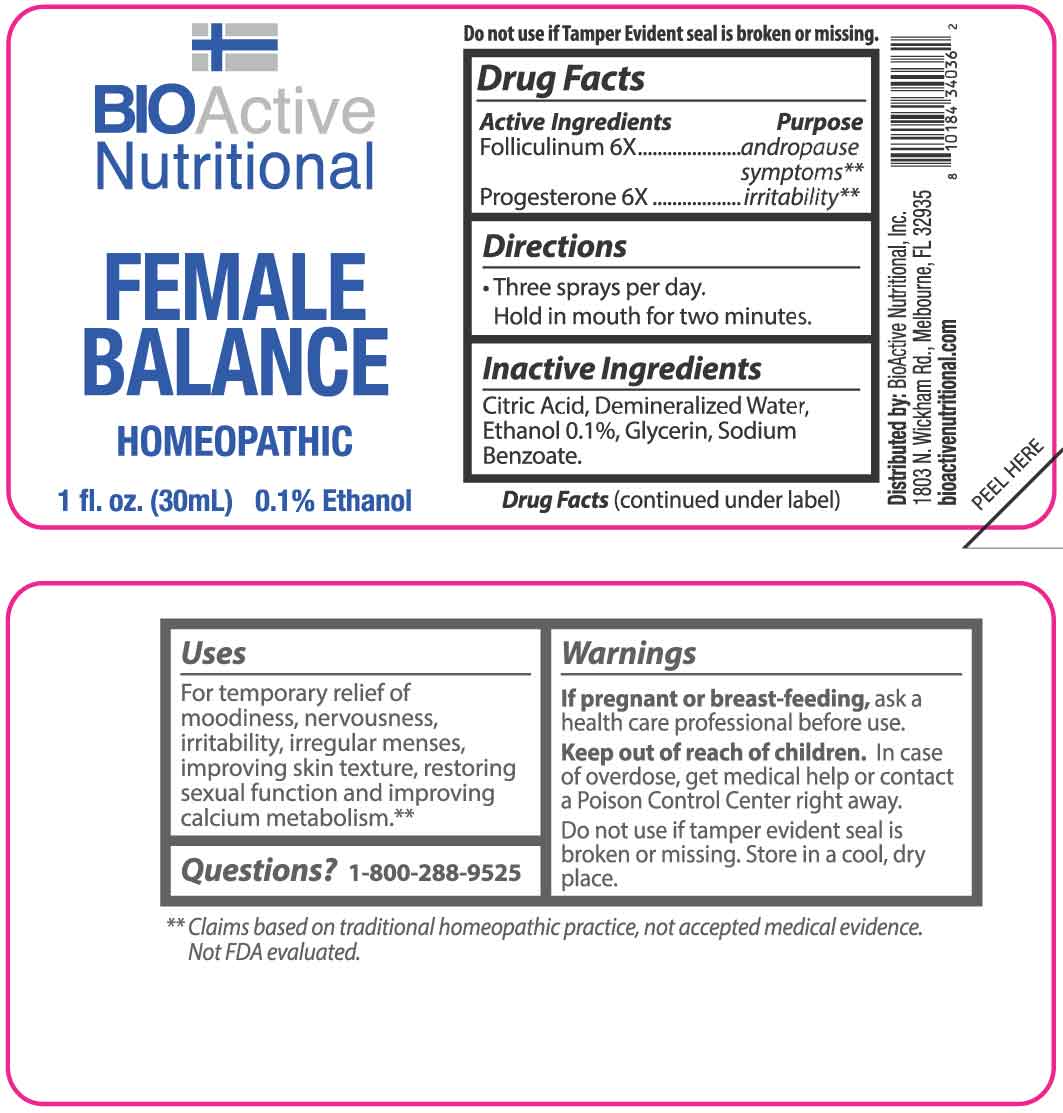 DRUG LABEL: FEMALE BALANCE
NDC: 43857-0180 | Form: LIQUID
Manufacturer: BioActive Nutritional, Inc.
Category: homeopathic | Type: HUMAN OTC DRUG LABEL
Date: 20251217

ACTIVE INGREDIENTS: ESTRONE 6 [hp_X]/1 mL; PROGESTERONE 6 [hp_X]/1 mL
INACTIVE INGREDIENTS: GLYCERIN; SODIUM BENZOATE; CITRIC ACID MONOHYDRATE; WATER

DRUG FACTS:

ACTIVE INGREDIENTS:

Folliculinum 6X, Progesterone 6X.

PURPOSE:

Folliculinum - andropause symptoms,** Progesterone - irritability**

**Claims based on traditional homeopathic practice, not accepted medical evidence. Not FDA evaluated.

USES:

For temporary relief of moodiness, nervousness, irritability, irregular menses, improving skin texture, restoring sexual function and improving calcium metabolism.**

**Claims based on traditional homeopathic practice, not accepted medical evidence. Not FDA evaluated.

WARNINGS:

If pregnant or breast-feeding, ask a health care professional before use.

Keep out of reach of children. In case of overdose, get medical help or contact a Poison Control Center right away.

Do not use if tamper evident seal is broken or missing.

Store in a cool, dry place.

KEEP OUT OF REACH OF CHILDREN:

In case of overdose, get medical help or contact a Poison Control Center right away.

DIRECTIONS:

• Three sprays per day.

Hold in mouth for two minutes.

INACTIVE INGREDIENTS:

Citric Acid, Demineralized Water, Ethanol 0.1%, Glycerin, Sodium Benzoate.

QUESTIONS:

Distributed by:
BioActive Nutritional, Inc.
1803 N. Wickham Rd.
Melbourne, FL 32935
bioactivenutritional.com

1-800-288-9525

PACKAGE LABEL DISPLAY:

BIOActive Nutritional

FEMALE BALANCE

HOMEOPATHIC

1 fl. oz. (30 mL)